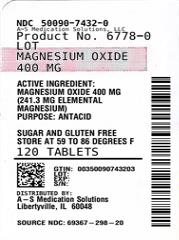 DRUG LABEL: Magnesium Oxide
NDC: 50090-7432 | Form: TABLET
Manufacturer: A-S Medication Solutions
Category: otc | Type: HUMAN OTC DRUG LABEL
Date: 20251010

ACTIVE INGREDIENTS: MAGNESIUM OXIDE 400 mg/1 1
INACTIVE INGREDIENTS: CELLULOSE, MICROCRYSTALLINE; CROSCARMELLOSE SODIUM; ZEA MAYS (CORN) STARCH; SILICA; STEARIC ACID

Magnesium Oxide

Drug Facts

Active Ingredient

Magnesium Oxide 400 mg (241.3 mg Elemental Magnesium)

Purpose

Antacid

Use

relieves:

- acid indigestion
- upset stomach

Warnings

Ask a doctor before use if

- you have kidney disease
- you are taking a prescription drug (antacids may interact with certain prescription drugs)
- you are pregnant or breast feeding.

DO NOT USE

Do not take more than 2 tablets in a 24 hour period.

- May have a laxative effect.

Keep out of reach of children.

Directions

- take one or two antacid tablets daily. Do not exceed two tablets unless directed by a physician.

Other Information

- Store at controlled room temperature 15° to 30°C (59° to 86°F).
- Tamper evident, do not use if imprinted safety seal under cap is broken or missing.

Inactive Ingredients

Colloidal Silicon Dioxide, Corn Starch, Croscarmellose Sodium, Microcrystalline Cellulose, and Stearic Acid.

Questions?

Call 1-844-221-7294 M-F 9am - 5pm EST

HOW SUPPLIED

Product: 50090-7432

NDC: 50090-7432-0 120 TABLET in a BOTTLE